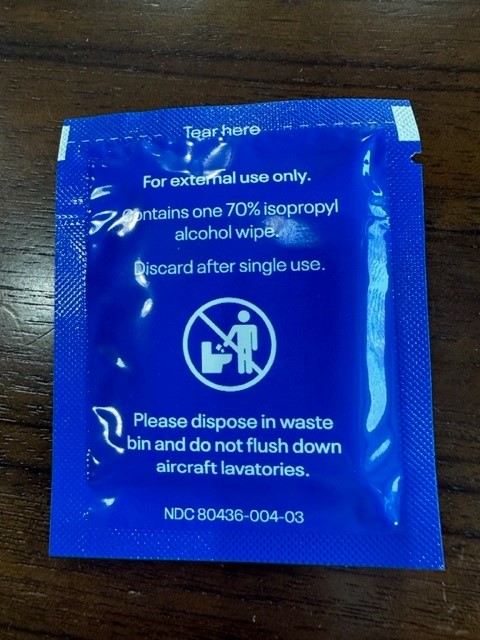 DRUG LABEL: United Sanitizing Wipe
NDC: 80436-006 | Form: CLOTH
Manufacturer: RMT Global Partners, LLC
Category: otc | Type: HUMAN OTC DRUG LABEL
Date: 20251221

ACTIVE INGREDIENTS: ISOPROPYL ALCOHOL 70 mL/100 mL
INACTIVE INGREDIENTS: WATER

RTM United Sanitizing Wipe

Active Ingredient(s)

Isopropyl Alcohol 70% v/v. Purpose: Antiseptic

Purpose

Antiseptic, Hand Sanitizer

Use

To reduce bacteria on the skin.

Warnings

For external use only. Flammable. Keep away from heat or flame

Do not use

On open skin wounds

Do not use in or near the eyes. In case of contact with eyes flush thoroughly with water.
Use wipes only on unbroken, intact skin
Do not ingest

STOP USE

If skin irritation or redness develops

Keep out of reach of children. If swallowed, get medical help or contact a Poison Control Center right away.

Directions

Wipe hands thoroughly, let skin dry and discard
Keep out of reach of children. Children under 6 years of age use only under adult supervision
Not recommended for infants
Do not store above 105°F

Inactive ingredients

pure water